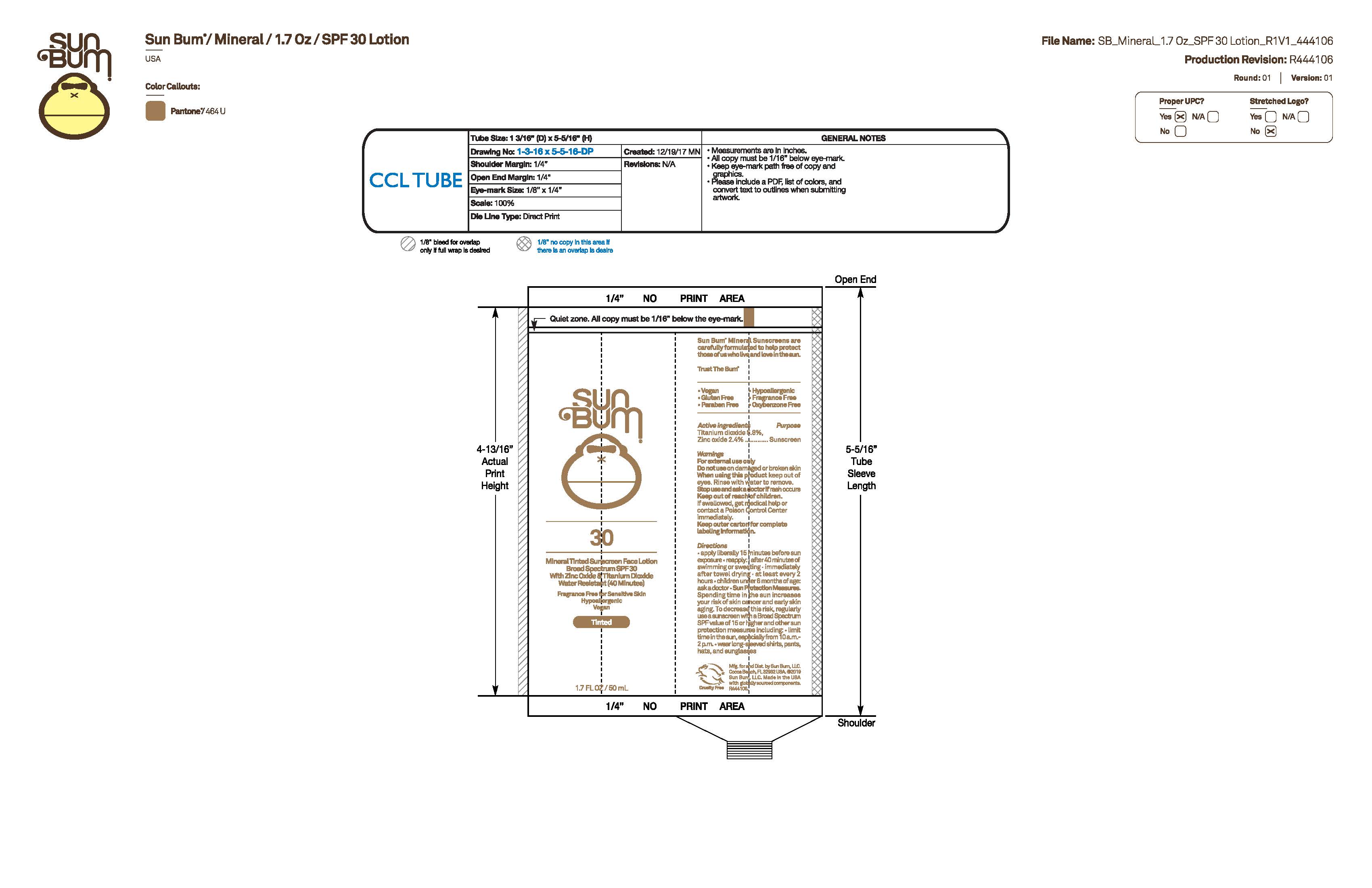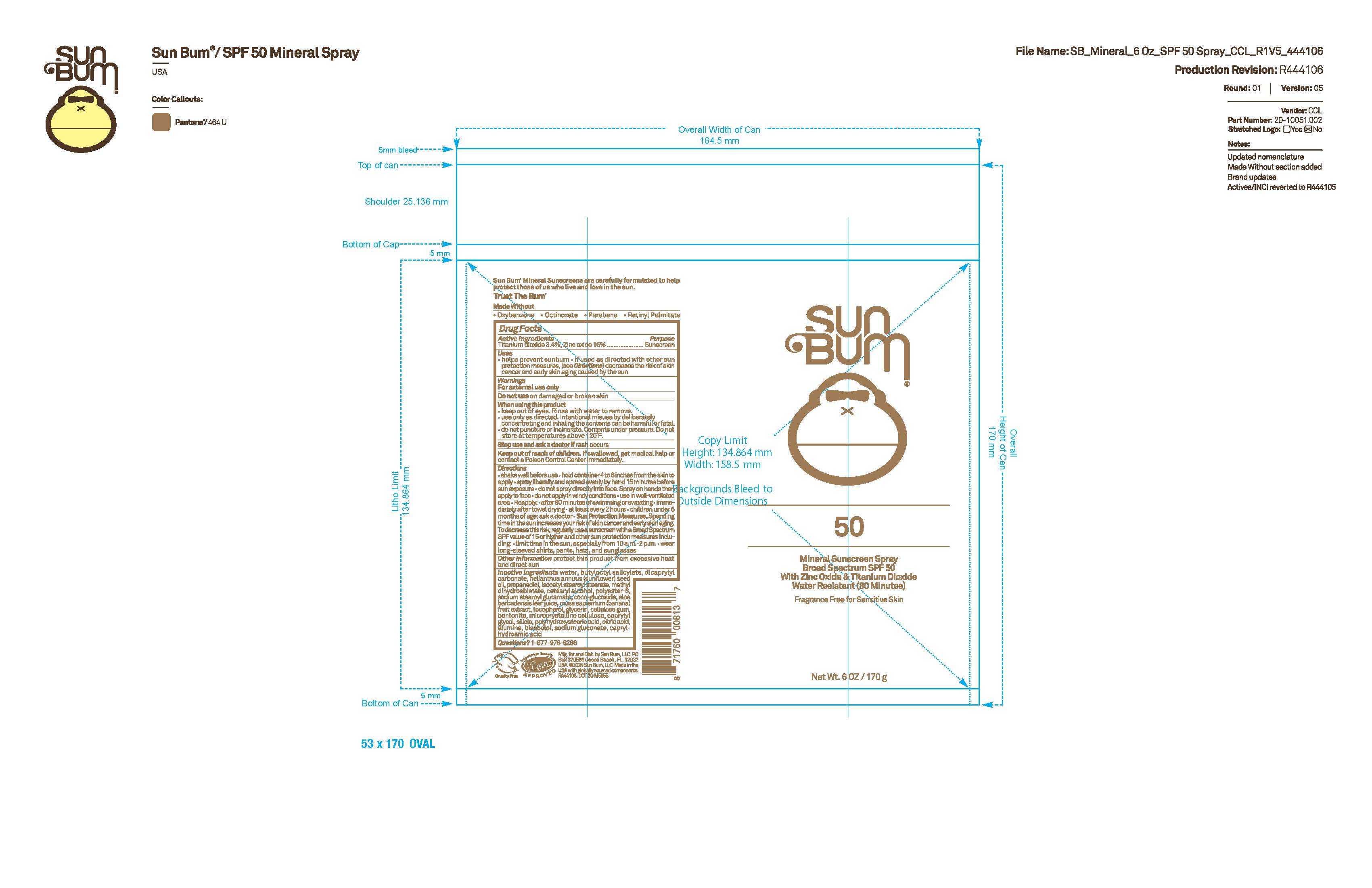 DRUG LABEL: Sun Bum 30 Mineral Tinted Sunscreen Face
NDC: 69039-734 | Form: LOTION
Manufacturer: Sun Bum, LLC
Category: otc | Type: HUMAN OTC DRUG LABEL
Date: 20250827

ACTIVE INGREDIENTS: ZINC OXIDE 24 mg/1 mL; TITANIUM DIOXIDE 58 mg/1 mL
INACTIVE INGREDIENTS: ORYZA SATIVA (RICE) BRAN; HELIANTHUS ANNUUS FLOWERING TOP; POLYAMIDE-5; TOCOPHEROL; ALUMINUM HYDROXIDE; DIMETHICONE/VINYL DIMETHICONE CROSSPOLYMER (SOFT PARTICLE); ROSEMARY; MICA; HYDROGEN DIMETHICONE (13 CST); DIMETHICONE CROSSPOLYMER; SILICA DIMETHYL SILYLATE; FERROUS OXIDE; ISOPROPYL TITANIUM TRIISOSTEARATE; OCTYLDODECYL OLEATE; CYCLOPENTASILOXANE; ISOPROPYL MYRISTATE; STEARALKONIUM HECTORITE; PROPYLENE CARBONATE; SYNTHETIC WAX (540 MW)

Sun Bum 30 Mineral Tinted Sunscreen Face

Active Ingredients

Titanium Dioxide 5.3%, Zinc Oxide 2.4%

Purpose

Sunscreen

Uses

• helps prevent sunburn • if used as directed with other sun protection measures, (see Directions) decreases the risk of skin cancer and early skin aging caused by the sun

Warnings

For external use only

Do not use on damaged or broken skin

When using this product keep out of eyes. Rinse with water to remove.

Stop use and ask a doctor if rash occurs

Keep out of reach of children. If swallowed, get medical help or contact a Poison Control Center immediately.

Keep outer carton for complete labeling information.

Warnings

Keep Out Of Reach Of Children

Directions

• apply liberally 15 minutes before sun exposure

• reapply: • after 40 minutes of swimming or sweating • immediately after towel drying • at least every 2 hours

• children under 6 months of age: ask a doctor

• Sun Protection Measures. Spending time in the sun increases your risk of skin cancer and early skin aging. To decrease this risk, regularly use a sunscreen with a Broad Spectrum SPF value of 15 or higher and other sun protection measures including:

• limit time in the sun, especially from 10 a.m.- 2 p.m.

• wear long-sleeved shirts, pants, hats and sunglasses

Directions

• apply liberally 15 minutes before sun exposure

Other Information

protect this product from excessive heat and direct sun

Inactive Ingredients

cyclopentasiloxane, isopropyl myristate, polyamide-5, dimethicone crosspolymer, stearalkonium hectorite, polysilicone-11, oryza sativa (rice) bran extract, rosmarinus officinalis (rosemary) leaf extract, helianthus annuus (sunflower) extract, tocopherol, mica, iron oxides, propylene carbonate, synthetic wax, hydrogen dimethicone, isopropyl titanium triisostearate, aluminum hydroxide, silica silylate, octyldodecyl oleate

Questions?

1-877-978-6286